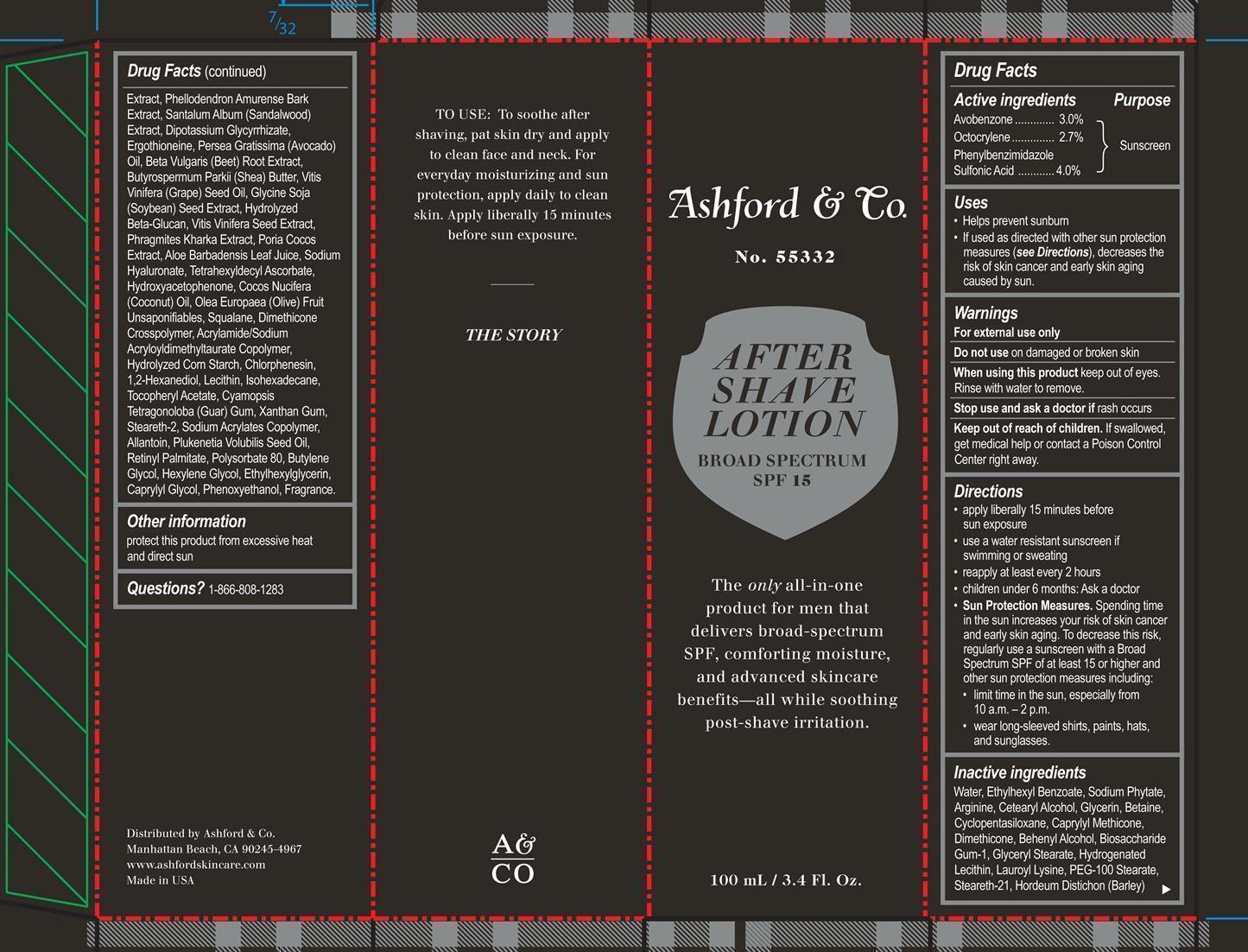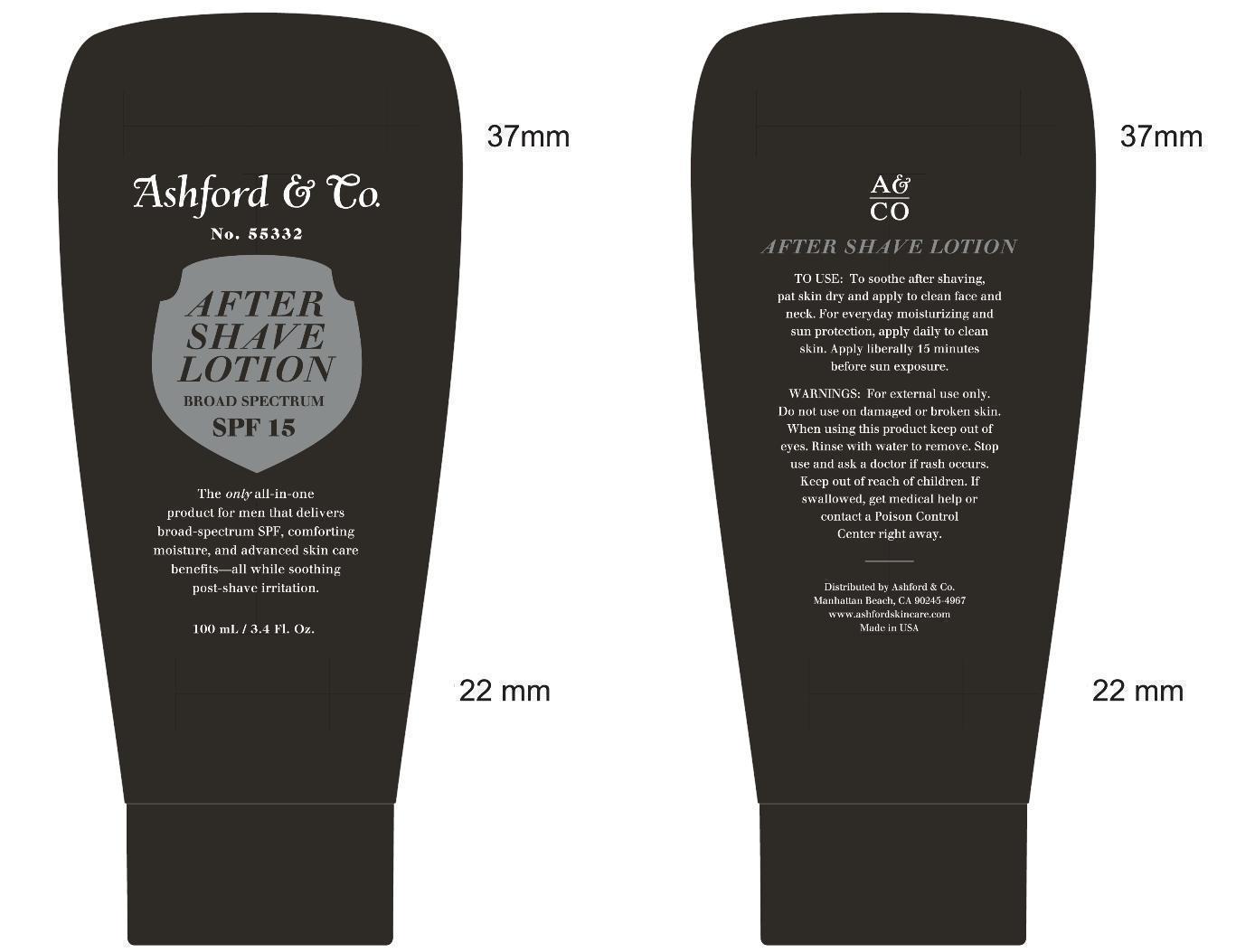 DRUG LABEL: After Shave  Broad Spectrum SPF 15
NDC: 24559-080 | Form: LOTION
Manufacturer: Dermstore, LLC
Category: otc | Type: HUMAN OTC DRUG LABEL
Date: 20150316

ACTIVE INGREDIENTS: AVOBENZONE 3 g/100 mL; OCTOCRYLENE 2.7 g/100 mL; ENSULIZOLE 4 g/100 mL
INACTIVE INGREDIENTS: WATER; 2-ETHYLHEXYL BENZOATE; PHYTATE SODIUM; ARGININE; CETOSTEARYL ALCOHOL; GLYCERIN; BETAINE; CYCLOMETHICONE 5; CAPRYLYL TRISILOXANE; DIMETHICONE; DOCOSANOL; BIOSACCHARIDE GUM-1; GLYCERYL MONOSTEARATE; HYDROGENATED SOYBEAN LECITHIN; LAUROYL LYSINE; PEG-100 STEARATE; STEARETH-21; BARLEY; PHELLODENDRON AMURENSE BARK; SANDALWOOD; GLYCYRRHIZINATE DIPOTASSIUM; ERGOTHIONEINE; AVOCADO OIL; BETA VULGARIS; VITIS VINIFERA SEED; SOYBEAN; FU LING; ALOE VERA LEAF; HYALURONATE SODIUM; TETRAHEXYLDECYL ASCORBATE; COCONUT OIL; SQUALANE; CHLORPHENESIN; 1,2-HEXANEDIOL; EGG PHOSPHOLIPIDS; ISOHEXADECANE; .ALPHA.-TOCOPHEROL ACETATE; GUAR GUM; XANTHAN GUM; STEARETH-2; ALLANTOIN; PLUKENETIA VOLUBILIS SEED OIL; VITAMIN A PALMITATE; POLYSORBATE 80; BUTYLENE GLYCOL; HEXYLENE GLYCOL; ETHYLHEXYLGLYCERIN; CAPRYLYL GLYCOL; PHENOXYETHANOL

Aftershave Broad Spectrum SPF 15

Active ingredients purpose

Avobenzone 3.0% Sunscreen

Octocrylene 2.75% Sunscreen

Phenylbenzimidazole Sulfonic Acid 4.0% Sunscreen

Uses
• Helps prevent sunburn
• If used as directed with other sun protection
measures (see Directions), decreases the
risk of skin cancer and early skin aging
caused by sun.

Keep out of reach of children. If Swallowed, get medical help or contact a Poison Control Center.

Stop use and ask a doctor if rash occurs

Warnings

For external use only.

Do not use on damaged or broken skin

When using this product keep out of eyes. Rinse with water to remove.

Directions

Apply liberally 15 minutes before sun exposure

Use a water resistant sunscreen if swimming or sweating

Reapply at least every 2 hours

children under 6 months: ask a doctor

Sun Protection Measures. Spending time in the sun increases your risk of skin cancer an early skin aging. To decrease this risk, regularly use a sunscreen with a Broad Spectrum of at least 15 or higher and other sun protection measures including:

limit time in the sun, especially from 10 a.m. - 2p.m.

Wear long-sleeved shirts, pants, hats, and sunglasses

INACTIVE INGREDIENT

Water, Ethylhexyl Benzoate, Sodium Phytate, Arginine, Cetearyl Alcohol, Glycerin, Betaine, Cyclopentasiloxane, Caprylyl Methicone, Dimethicone, Behenyl Alcohol, Biosaccharide Gum-1, Glyceryl Stearate, Hydrogenated Lecithin, Lauroyl Lysine, PEG-100 Stearate, Steareth-21, Hordeum Distichon (Barley) Extract, Phellodendron Amurense Bark Extract, Santalum Album (Sandalwood) Extract, Dipotassium Glycyrrhizate, Ergothioneine, Persea Gratissima (Avocado) Oil, Beta Vulgaris (Beet) Root Extract, Butyrospermum Parkii (Shea) Butter, Vitis Vinifera (Grape) Seed Oil, Glycine Soja (Soybean) Seed Extract, Hydrolyzed Beta-Glucan, Vitis Vinifera Seed Extract, Phragmites Kharka Extract, Poria Cocos Extract, Aloe Barbadensis Leaf Juice, Sodium Hyaluronate, Tetrahexyldecyl Ascorbate, Hydroxyacetophenone, Cocos Nucifera (Coconut) Oil, Olea Europaea (Olive) Fruit Unsaponifiables, Squalane, Dimethicone Crosspolymer, Acrylamide/Sodium Acryloyldimethyltaurate Copolymer, Hydrolyzed Corn Starch, Chlorphenesin, 1,2-Hexanediol, Lecithin, Isohexadecane, Tocopheryl Acetate, Cyamopsis Tetragonoloba (Guar) Gum, Xanthan Gum, Steareth-2, Sodium Acrylates Copolymer, Allantoin, Plukenetia Volubilis Seed Oil, Retinyl Palmitate, Polysorbate 80, Butylene Glycol, Hexylene Glycol, Ethylhexylglycerin, Caprylyl Glycol, Phenoxyethanol, Fragrance.

PACKAGE LABEL

Ashford & Co

No. 55332

After Shave Lotion Broad Spectrum SPF 15

100 mL/ 3.4 Fl. Oz.